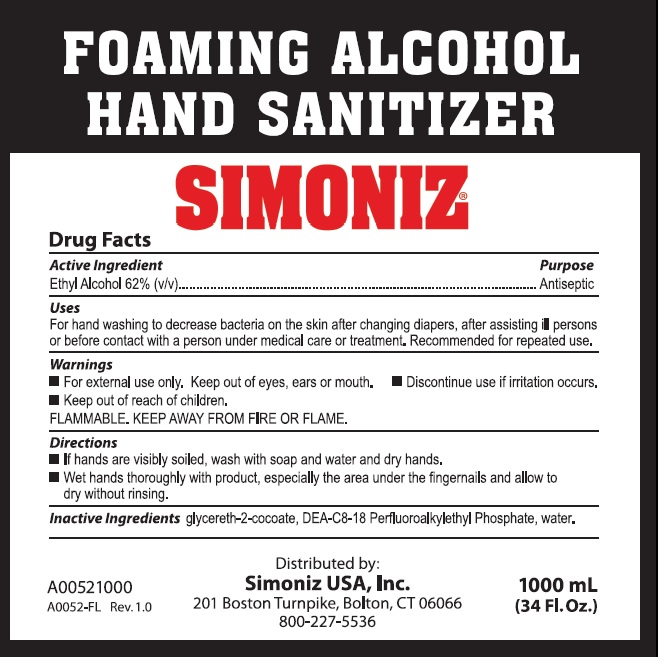 DRUG LABEL: Foaming Alcohol Hand Sanitizer
NDC: 63900-002 | Form: LIQUID
Manufacturer: Simoniz USA, Inc
Category: otc | Type: HUMAN OTC DRUG LABEL
Date: 20231028

ACTIVE INGREDIENTS: ALCOHOL 0.62 mL/1 mL
INACTIVE INGREDIENTS: GLYCERETH-2 COCOATE; DIETHANOLAMINE BIS(C8-C18 PERFLUOROALKYLETHYL)PHOSPHATE; WATER

Foaming Alcohol Hand Sanitizer

Active Ingredient

Ethyl Alcohol 62% (v/v)

Purpose

Antiseptic

Use

For handwashing to decrease bacteria on the skin after changing diapers, after assisting ill persons or before contact with a person under medical care or treatment. Recommended for repeated use.

Warnings

- For external use only. Keep out of eyes, ears or mouth.

- Discontinue use if irritation occurs

- Keep out of reach of children

FLAMMABLE. KEEP AWAY FROM FIRE OR FLAME

Directions

- If hands are visibily soiled, wash with soap and water and dry hands.
- Wet hands thoroughly with product, especially the area under the fingernails and allow to dry without rinsing.

Other Information

- Store between 59-86°F (15-30°C)
- Avoid freezing and excessive heat above 104°F (40°C)

Inactive ingredients

glycereth-2-cocoate, DEA-C8-18 Perfluroalkylethyl Phosphate, water.